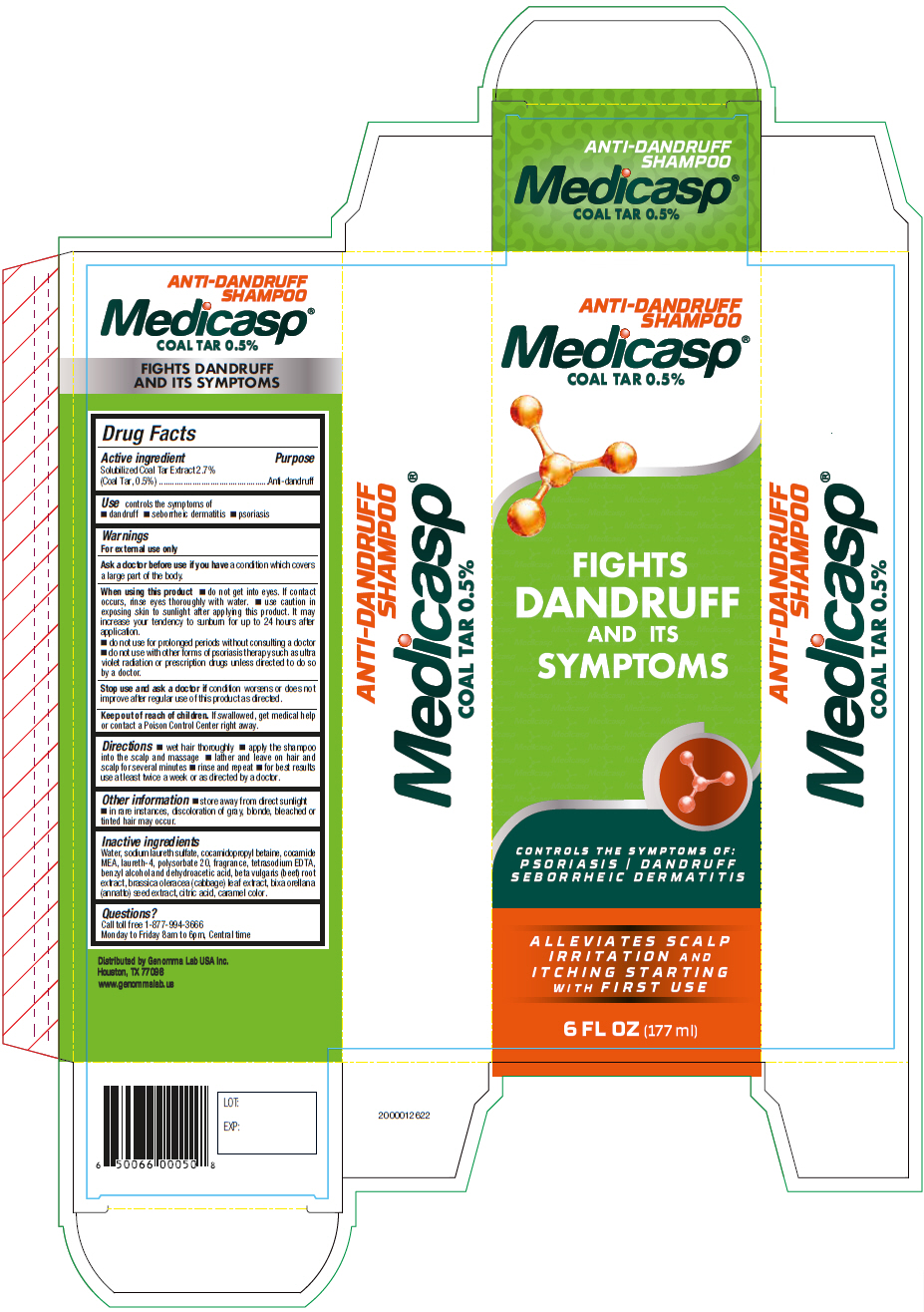 DRUG LABEL: Medicasp Anti-Dandruff
NDC: 50066-040 | Form: LIQUID
Manufacturer: Genomma Lab USA
Category: otc | Type: HUMAN OTC DRUG LABEL
Date: 20251204

ACTIVE INGREDIENTS: COAL TAR 5 mg/1 mL
INACTIVE INGREDIENTS: water; SODIUM LAURETH-3 SULFATE; cocamidopropyl betaine; COCO MONOETHANOLAMIDE; laureth-4; polysorbate 20

Medicasp® Anti-Dandruff Shampoo

Drug Facts

Active ingredient

Solubilized Coal Tar Extract 2.7% (Coal Tar, 0.5%)

Purpose

Anti-dandruff

Use

controls the symptoms of

- dandruff
- seborrheic dermatitis
- psoriasis

Warnings

For external use only

Ask a doctor before use if you have a condition which covers a large part of the body.

When using this product

- do not get into eyes. If contact occurs, rinse eyes thoroughly with water.
- use caution in exposing skin to sunlight after applying this product. It may increase your tendency to sunburn for up to 24 hours after application.
- do not use for prolonged periods without consulting a doctor
- do not use with other forms of psoriasis therapy such as ultra violet radiation or prescription drugs unless directed to do so by a doctor.

Stop use and ask a doctor if condition worsens or does not improve after regular use of this product as directed.

Keep out of reach of children. If swallowed, get medical help or contact a Poison Control Center right away.

Directions

- wet hair thoroughly
- apply the shampoo into the scalp and massage
- lather and leave on hair and scalp for several minutes
- rinse and repeat
- for best results use at least twice a week or as directed by a doctor.

Other information

- store away from direct sunlight
- in rare instances, discoloration of gray, blonde, bleached or tinted hair may occur.

Inactive ingredients

Water, sodium laureth sulfate, cocamidopropyl betaine, cocamide MEA, laureth-4, polysorbate 20, fragrance, tetrasodium EDTA, benzyl alcohol and dehydroacetic acid, beta vulgaris (beet) root extract, brassica oleracea (cabbage) leaf extract, bixa orellana (annatto) seed extract, citric acid, caramel color.

Questions?

Call toll free 1-877-994-3666

Monday to Friday 8am to 6pm, Central time

Distributed by Genomma Lab USA Inc.
Houston, TX 77098

PRINCIPAL DISPLAY PANEL - 177 ml Bottle Carton

ANTI-DANDRUFF
SHAMPOO

Medicasp®
COAL TAR 0.5%

FIGHTS
DANDRUFF
AND ITS
SYMPTOMS

CONTROLS THE SYMPTOMS OF:
PSORIASIS / DANDRUFF
SEBORRHEIC DERMATITIS

ALLEVIATES SCALP
IRRITATION AND
ITCHING STARTING
WITH FIRST USE

6 FL OZ (177 ml)